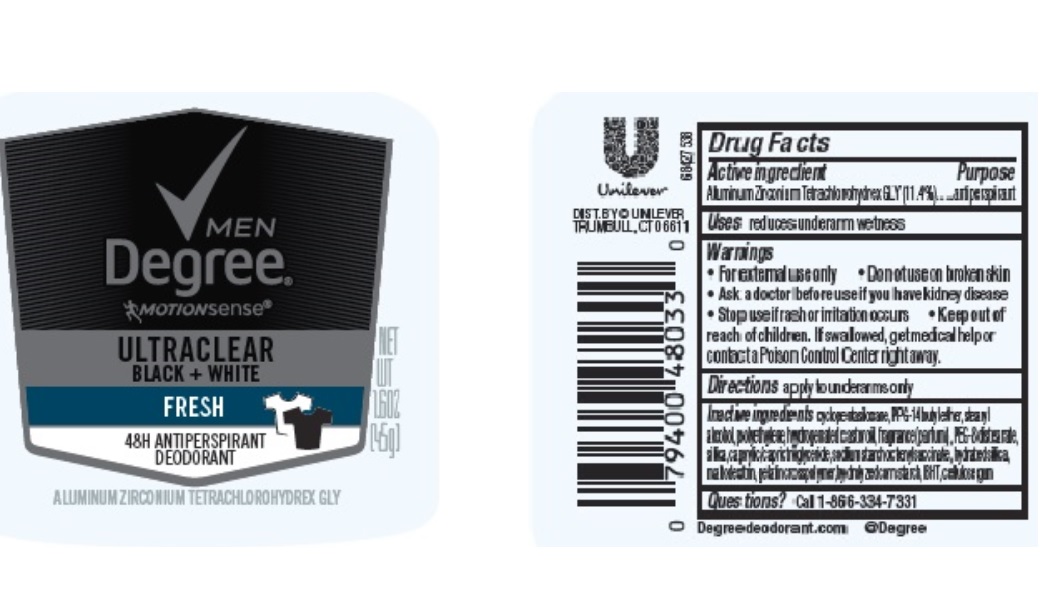 DRUG LABEL: Degree
NDC: 64942-1795 | Form: STICK
Manufacturer: Conopco Inc. d/b/a/ Unilever
Category: otc | Type: HUMAN OTC DRUG LABEL
Date: 20241110

ACTIVE INGREDIENTS: ALUMINUM ZIRCONIUM TETRACHLOROHYDREX GLY 11.4 g/100 g
INACTIVE INGREDIENTS: HIGH DENSITY POLYETHYLENE; HYDRATED SILICA; CYCLOMETHICONE 5; HYDROGENATED CASTOR OIL; BUTYLATED HYDROXYTOLUENE; PPG-14 BUTYL ETHER; STEARYL ALCOHOL; MALTODEXTRIN; SILICON DIOXIDE; CARBOXYMETHYLCELLULOSE SODIUM, UNSPECIFIED FORM; PEG-8 DISTEARATE; MEDIUM-CHAIN TRIGLYCERIDES

Degree Men Fresh Ultraclear Black & White 48H Antiperspirant Deodorant

DEGREE MEN FRESH ULTRACLEAR BLACK & WHITE 48H ANTIPERSPIRANT DEODORANT - aluminum zirconium tetrachlorohydrex gly

Degree Men Fresh Ultraclear Black & White 48H Antiperspirant Deodorant

Drug Facts

Active ingredient

Aluminum Zirconium Tetrachlorohydrex GLY (11.4 %)

Purpose

antiperspirant

Uses

reduces underarm wetness

Warnings

• For external use only.
• Do not use on broken skin .
• Ask a doctor before use if you have kidney disease.
• Stop use if rash or irritation occurs.

• Keep out of reach of children.

If swallowed, get medical help or contact a Poison Control Center right away.

Directions

apply to underarms only

Inactive ingredients

Cyclopentasiloxane, PPG-14 Butyl Ether, Stearyl Alcohol, Polyethylene, Hydrogenated Castor Oil, Fragrance (Parfum), PEG-8 Distearate, Silica, Caprylic/Capric Triglyceride, Sodium Starch Octenylsuccinate, Hydrated Silica, Maltodextrin, Gelatin Crosspolymer, Hydrolyzed Corn Starch, BHT, Cellulose Gum

Questions?

Call toll-free 1-866-334-7331